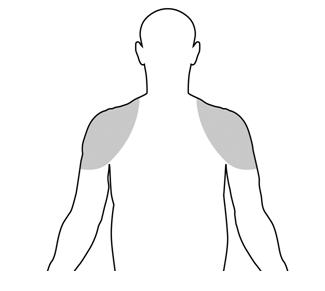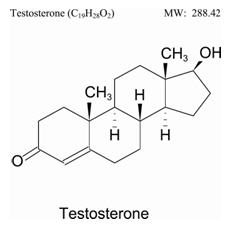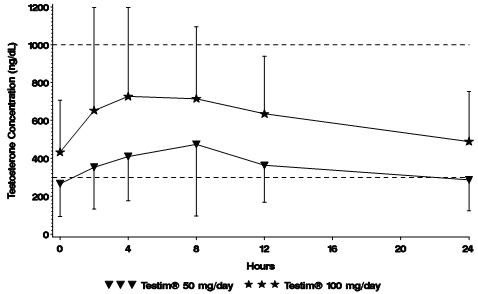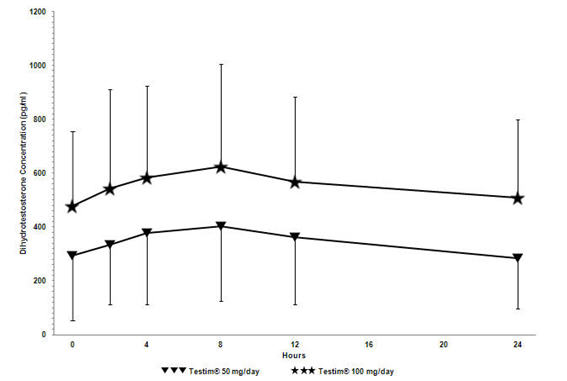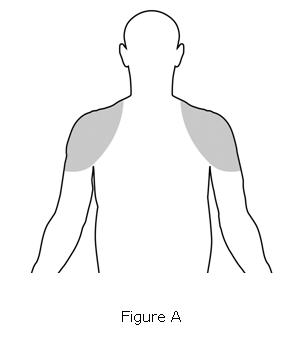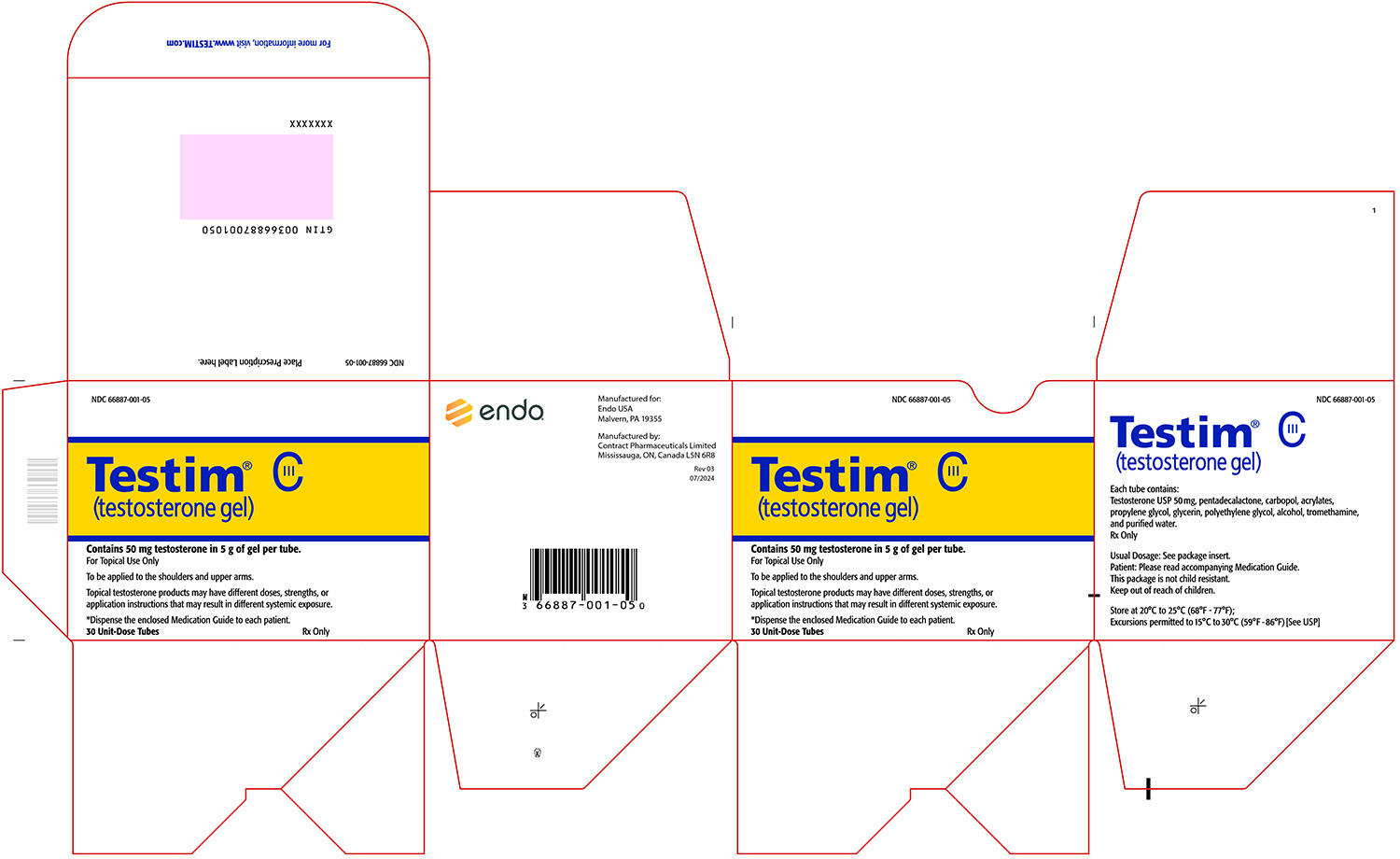 DRUG LABEL: Testim
NDC: 66887-001 | Form: GEL
Manufacturer: Endo USA, Inc.
Category: prescription | Type: HUMAN PRESCRIPTION DRUG LABEL
Date: 20250715
DEA Schedule: CIII

ACTIVE INGREDIENTS: TESTOSTERONE 50 mg/5 g

HIGHLIGHTS OF PRESCRIBING INFORMATION

These highlights do not include all the information needed to use TESTIM® safely and effectively. See full prescribing information for TESTIM®.
TESTIM® (testosterone gel) for topical use, CIII
Initial U.S. Approval: 1953

WARNING: SECONDARY EXPOSURE TO TESTOSTERONE

See full prescribing information for complete boxed warning.

- Virilization has been reported in children who were secondarily exposed to testosterone gel (5.1, 6.2)
- Children should avoid contact with unwashed or unclothed application sites in men using testosterone gel (2.2, 5.1)
- Healthcare providers should advise patients to strictly adhere to recommended instructions for use (2.2, 5.1, 17)

1 INDICATIONS AND USAGE

TESTIM is an androgen indicated for testosterone replacement therapy in males for conditions associated with a deficiency or absence of endogenous testosterone:

- Primary Hypogonadism (Congenital or Acquired) (1)
- Hypogonadotropic Hypogonadism (1)

Limitations of Use:

- Safety and efficacy of TESTIM in men with “age-related hypogonadism” have not been established. (1)
- Safety and efficacy of TESTIM in males less than 18 years old have not been established. (8.4)
- Topical testosterone products may have different doses, strengths, or application instructions that may result in different systemic exposure. (1, 12.3)

RECENT MAJOR CHANGES

Warnings and Precautions, Venous Thromboembolism (5.3) 07/2025

Warnings and Precautions, Blood Pressure Increases (5.5) 07/2025

Warnings and Precautions, Cardiovascular Risk (5.5) Removed 07/2025

2 DOSAGE AND ADMINISTRATION

- Prior to initiating TESTIM, confirm the diagnosis of hypogonadism by ensuring that serum testosterone has been measured in the morning on at least two separate days and that these concentrations are below the normal range. (2)
- Recommended starting dose for adult males: 50 mg of testosterone (one tube) applied topically once daily. (2.1)
- Apply to clean, dry, intact skin of the shoulders and/or upper arms. Do NOT apply TESTIM to the genitals or abdomen. (2.1, 2.2)
- If morning pre-dose serum testosterone concentration is below normal range, increase dose to 100 mg. (2.1)
- Pre-dose serum testosterone concentration should be assessed periodically. (2.1)
- Patients should wash hands with soap and water immediately after applying TESTIM and cover application site(s) with clothing after gel has dried. Wash the application site thoroughly with soap and water prior to any situation where skin-to-skin contact of the application site with another person is anticipated. (2.2)
- TESTIM is not substitutable with other topical testosterone products. (2.1)

3 DOSAGE FORMS AND STRENGTHS

Topical gel: 50 mg of testosterone in a unit-dose tube (3)

4 CONTRAINDICATIONS

- Men with known carcinoma of the breast or known or suspected carcinoma of the prostate. (4, 5.4)
- Women who are pregnant. Testosterone may cause fetal harm. (4, 5.7, 8.1, 8.2)

5 WARNINGS AND PRECAUTIONS

- Potential for Secondary Exposure to Testosterone: Avoid unintentional exposure of women or children to TESTIM. Secondary exposure to testosterone can produce signs of virilization. TESTIM should be discontinued until the cause of virilization is identified. (5.1)
- Venous thromboembolism (VTE): VTE, including deep vein thrombosis (DVT) and pulmonary embolism (PE), have been reported in patients using testosterone products. Evaluate patients with signs or symptoms consistent with DVT or PE. (5.3)
- Worsening of Benign Prostatic Hyperplasia (BPH) and Potential Risk of Prostate Cancer: Monitor patients with benign prostatic hyperplasia (BPH) for worsening of signs and symptoms of BPH. (5.4)
- Blood Pressure Increases: Testosterone can increase blood pressure, which can increase cardiovascular risk over time. Measure blood pressure periodically. Not recommended for use in men with uncontrolled hypertension (5.5)
- Abuse of Testosterone: Testosterone has been subject to abuse, typically at doses higher than recommended for the approved indication and in combination with other anabolic androgenic steroids (5.6).
- Potential for Adverse Effects on Spermatogenesis
- Exogenous administration of androgens may lead to azoospermia. (5.8)
- Edema: Edema, with or without congestive heart failure, may be a complication in patients with preexisting cardiac, renal, or hepatic disease. (5.10, 6.2)
- Sleep apnea: Sleep apnea may occur in those with risk factors. (5.12)
- Monitor prostate specific antigen (PSA), hematocrit, and lipid concentrations periodically. (5.2, 5.4, 5.13)
- TESTIM is flammable until dry. (5.16)

6 ADVERSE REACTIONS

Most common adverse reactions (incidence ≥ 2% of the TESTIM patients and greater than placebo) are application site reaction and increased hematocrit. (6.1)

To report SUSPECTED ADVERSE REACTIONS, contact Endo at 1-800-462-3636 or FDA at 1-800-FDA-1088 or www.fda.gov/medwatch.

7 DRUG INTERACTIONS

- Androgens may decrease blood glucose and therefore may decrease insulin requirements in diabetic patients. (7.1)
- Changes in anticoagulant activity may be seen with androgens. More frequent monitoring of international normalized ratio (INR) and prothrombin time is recommended in patients taking warfarin. (7.2)
- Use of testosterone with corticosteroids may result in increased fluid retention. Use with caution, particularly in patients with cardiac, renal, or hepatic disease. (7.3)

8 USE IN SPECIFIC POPULATIONS

Geriatric Patients: There are insufficient long-term safety data to assess the potential risks of cardiovascular disease and prostate cancer. (8.5)

FULL PRESCRIBING INFORMATION

WARNING: SECONDARY EXPOSURE TO TESTOSTERONE

- Virilization has been reported in children who were secondarily exposed to testosterone gel [see Warnings and Precautions (5.1) and Adverse Reactions (6.2)].
- Children should avoid contact with unwashed or unclothed application sites in men using testosterone gel [see Dosage and Administration (2.2) and Warnings and Precautions (5.1)].
- Healthcare providers should advise patients to strictly adhere to recommended instructions for use [see Dosage and Administration (2.2), Warnings and Precautions (5.1), and Patient Counseling Information (17)].

1 INDICATIONS AND USAGE

TESTIM is indicated for testosterone replacement therapy in adult males for conditions associated with a deficiency or absence of endogenous testosterone:

- Primary hypogonadism (congenital or acquired): testicular failure due to cryptorchidism, bilateral torsion, orchitis, vanishing testis syndrome, orchiectomy, Klinefelter's syndrome, chemotherapy, or toxic damage from alcohol or heavy metals. These men usually have low serum testosterone concentrations and gonadotropins (follicle-stimulating hormone [FSH], luteinizing hormone [LH]) above the normal range.
- Hypogonadotropic hypogonadism (congenital or acquired): gonadotropin or luteinizing hormone-releasing hormone (LHRH) deficiency or pituitary-hypothalamic injury from tumors, trauma, or radiation. These men have low testosterone serum concentrations but have gonadotropins in the normal or low range.

Limitations of Use:

- Safety and efficacy of TESTIM in men with “age-related hypogonadism” (also referred to as “late-onset hypogonadism”) have not been established.
- Safety and efficacy of TESTIM in males less than 18 years old have not been established [see Use in Specific Populations (8.4)].
- Topical testosterone products may have different doses, strengths, or application instructions that may result in different systemic exposure [see Dosage and Administration (2) and Clinical Pharmacology (12.3)].

RECENT MAJOR CHANGES

Warnings and Precautions, Venous Thromboembolism (5.3) 07/2025

Warnings and Precautions, Blood Pressure Increases (5.5) 07/2025

Warnings and Precautions, Cardiovascular Risk (5.5) Removed 07/2025

2 DOSAGE AND ADMINISTRATION

Prior to initiating TESTIM, confirm the diagnosis of hypogonadism by ensuring that serum testosterone concentrations have been measured in the morning on at least two separate days and that these serum testosterone concentrations are below the normal range.

2.1 Dosing and Dose Adjustment

The recommended starting dose of TESTIM is 50 mg of testosterone (one tube) applied once daily (preferably in the morning) to clean, dry intact skin of the shoulders and/or upper arms.

Dose Adjustment

To ensure proper dosing, serum testosterone concentrations should be measured. Morning, pre-dose serum testosterone concentrations should be measured approximately 14 days after initiation of therapy to ensure proper serum testosterone concentrations are achieved. If the serum testosterone concentration is below the normal range (300 ng/dL to 1,000 ng/dL), the daily TESTIM dose may be increased from 50 mg testosterone (one tube) to 100 mg testosterone (two tubes) once daily.

The maximum recommended dose of TESTIM is 100 mg once daily.

The application site and dose of TESTIM are not substitutable with other topical testosterone products.

2.2 Administration Instructions

Upon opening the tube the entire contents should be squeezed into the palm of the hand and immediately applied to the shoulders and/or upper arms (area of application should be limited to the area that will be covered by the patient’s short sleeve T-shirt (see figure below). Do not apply TESTIM to the genitals or to the abdomen.

Application sites should be allowed to dry for a few minutes prior to dressing. Hands should be washed thoroughly with soap and water after TESTIM has been applied. Avoid fire, flame or smoking during the application of TESTIM until the TESTIM has dried [see Warnings and Precautions (5.1, 5.16)].

In order to prevent transfer to another person, wear clothing to cover the application sites. If direct skin-to-skin contact with another person is anticipated, the application sites must be washed thoroughly with soap and water [see Warnings and Precautions (5.1) and Clinical Pharmacology (12.3)].

The patient should avoid swimming or showering or washing the administration site for a minimum of 2 hours after application [see Clinical Pharmacology (12.3)].

Strict adherence to the following precautions is advised in order to minimize the potential for secondary exposure to testosterone from TESTIM-treated skin:

- Children and women should avoid contact with unwashed or unclothed application site(s) of men using TESTIM.
- TESTIM should only be applied to the upper arms and shoulders. The area of application should be limited to the area that will be covered by a short sleeve T-shirt.
- Patients should wash their hands with soap and water immediately after applying TESTIM.
- Patients should cover the application site(s) with clothing (e.g., a T-shirt) after the gel has dried.
- Prior to situations in which direct skin-to-skin contact is anticipated, patients should wash the application site(s) thoroughly with soap and water to remove any testosterone residue.
- In the event that unwashed or unclothed skin to which TESTIM has been applied comes in direct contact with the skin of another person, the general area of contact on the other person should be washed with soap and water as soon as possible.

3 DOSAGE FORMS AND STRENGTHS

TESTIM (testosterone gel) for topical use is available in a unit-dose tube. Each tube contains 50 mg testosterone in 5 g of gel.

4 CONTRAINDICATIONS

- TESTIM is contraindicated in men with carcinoma of the breast or known or suspected carcinoma of the prostate [see Warnings and Precautions (5.4)].
- TESTIM is contraindicated in women who are pregnant. Testosterone can cause virilization of the female fetus when administered to a pregnant woman [see Use in Specific Populations (8.1, 8.2)].

5 WARNINGS AND PRECAUTIONS

5.1 Potential for Secondary Exposure to Testosterone

Cases of secondary exposure resulting in virilization of children have been reported in postmarketing surveillance. Signs and symptoms have included enlargement of the penis or clitoris, development of pubic hair, increased erections and libido, aggressive behavior, and advanced bone age. In most cases, these signs and symptoms regressed with removal of the exposure to testosterone gel. In a few cases, however, enlarged genitalia did not fully return to age-appropriate normal size, and bone age remained modestly greater than chronological age. The risk of transfer was increased in some of these cases by not adhering to precautions for the appropriate use of the topical testosterone product. Children and women should avoid contact with unwashed or unclothed application sites in men using TESTIM [see Dosage and Administration (2.2), Use in Specific Populations (8.1), and Clinical Pharmacology (12.3)].

Inappropriate changes in genital size or development of pubic hair or libido in children, or changes in body hair distribution, significant increase in acne, or other signs of virilization in adult women should be brought to the attention of a physician and the possibility of secondary exposure to testosterone gel should also be brought to the attention of a physician. Testosterone gel should be promptly discontinued until the cause of virilization has been identified.

5.2 Polycythemia

Increases in hematocrit, reflective of increases in red blood cell mass, may require lowering or discontinuation of testosterone. Check hematocrit prior to initiating treatment. It would also be appropriate to re-evaluate the hematocrit 3 to 6 months after starting treatment, and then annually. If hematocrit becomes elevated, stop therapy until hematocrit decreases to an acceptable concentration. An increase in red blood cell mass may increase the risk of thromboembolic events.

5.3 Venous Thromboembolism (VTE)

There have been postmarketing reports of venous thromboembolic events, including deep vein thrombosis (DVT) and pulmonary embolism (PE), in patients using testosterone products, such as TESTIM.

In the Testosterone Replacement therapy for Assessment of long-term Vascular Events and efficacy ResponSE in hypogonadal men (TRAVERSE) Study, a randomized, double-blind, placebo-controlled, cardiovascular (CV) outcomes study, compared to placebo, topical testosterone gel was associated with a numerically higher incidence of VTE (1.7% vs 1.2%) which included DVT (0.6% vs 0.5%) and PE events (0.9% vs 0.5%) [see Adverse Reactions (6.1)].

Evaluate patients who report symptoms of pain, edema, warmth and erythema in the lower extremity for DVT and those who present with acute shortness of breath for PE. If a venous thromboembolic event is suspected, discontinue treatment with TESTIM and initiate appropriate workup and management [see Adverse Reactions (6.2)].

5.4 Worsening of Benign Prostatic Hyperplasia (BPH) and Potential Risk of Prostate Cancer

- Patients with BPH treated with androgens are at an increased risk for worsening of signs and symptoms of BPH. Monitor patients with BPH for worsening signs and symptoms.
- Patients treated with androgens may be at increased risk for prostate cancer. Evaluate patients for prostate cancer prior to initiating and during treatment with androgens [see Contraindications (4)].

5.5 Blood Pressure Increases

TESTIM can increase blood pressure. In an ambulatory blood pressure monitoring (ABPM) study, TESTIM increased the mean systolic/diastolic blood pressure by 2.7/1.1 mm Hg from baseline after 16 weeks of treatment. In patients with hypertension on antihypertensive therapy, TESTIM increased the mean systolic/diastolic BP by 1.9/0.3 mm Hg from baseline. Blood pressure increases can increase cardiovascular (CV) risk over time.

The CV risk associated with topical testosterone gel was evaluated in TRAVERSE, a randomized, double-blind, placebo-controlled, CV outcomes study in men with a history of CV disease or multiple CV risk factors. In TRAVERSE, topical testosterone gel increased mean systolic blood pressure by 1.0 mm Hg from baseline to 36 months, whereas a mean decrease from baseline of 0.5 mm Hg was observed in the placebo group at this timepoint, for a mean between-group difference of 1.5 mm Hg. However, the incidences of major adverse cardiovascular events (MACE), including cardiovascular death, non-fatal myocardial infarction [MI] and non-fatal stroke, were similar between treatment groups (7% for topical testosterone gel vs 7.3% for placebo) [See Adverse Reactions (6.1)].

Monitor blood pressure periodically in men using TESTIM, especially men with hypertension. TESTIM is not recommended for use in patients with uncontrolled hypertension.

5.6 Abuse of Testosterone and Monitoring of Serum Testosterone Concentrations

Testosterone has been subject to abuse, typically at doses higher than recommended for the approved indication and in combination with other anabolic androgenic steroids. Anabolic androgenic steroid abuse can lead to serious cardiovascular and psychiatric adverse reactions [see Drug Abuse and Dependence (9)].

If testosterone abuse is suspected, check serum testosterone concentrations to ensure they are within therapeutic range. However, testosterone levels may be in the normal or subnormal range in men abusing synthetic testosterone derivatives. Counsel patients concerning the serious adverse reactions associated with abuse of testosterone and anabolic androgenic steroids. Conversely, consider the possibility of testosterone and anabolic androgenic steroid abuse in suspected patients who present with serious cardiovascular or psychiatric adverse events.

5.7 Not for Use in Women

Due to lack of controlled evaluations in women and potential virilizing effects, TESTIM is not indicated for use in women [see Contraindications (4) and Use in Specific Populations (8.1, 8.2)].

5.8 Potential for Adverse Effects on Spermatogenesis

With large doses of exogenous androgens, including TESTIM, spermatogenesis may be suppressed through feedback inhibition of pituitary follicle-stimulating hormone (FSH) which could possibly lead to adverse effects on semen parameters including sperm count.

5.9 Hepatic Adverse Effects

Prolonged use of high doses of orally active 17-alpha-alkyl androgens (e.g., methyltestosterone) has been associated with serious hepatic adverse effects (peliosis hepatis, hepatic neoplasms, cholestatic hepatitis, and jaundice). Peliosis hepatis can be a life-threatening or fatal complication. Long-term therapy with intramuscular testosterone enanthate, which elevates blood levels for prolonged periods, has produced multiple hepatic adenomas. TESTIM is not known to cause these adverse effects. Nonetheless, patients should be instructed to report any signs or symptoms of hepatic dysfunction (e.g., jaundice). If these occur, promptly discontinue TESTIM while the cause is evaluated.

5.10 Edema

Androgens, including TESTIM, may promote retention of sodium and water. Edema, with or without congestive heart failure, may be a serious complication in patients with preexisting cardiac, renal, or hepatic disease. In addition to discontinuation of the drug, diuretic therapy may be required.

5.11 Gynecomastia

Gynecomastia occasionally develops and occasionally persists in patients being treated for hypogonadism [see Adverse Reactions (6.1)].

5.12 Sleep Apnea

The treatment of hypogonadal men with testosterone may potentiate sleep apnea in some patients, especially those with risk factors such as obesity or chronic lung diseases.

5.13 Lipid Changes

Changes in the serum lipid profile may occur. Monitor the lipid profile periodically, particularly after starting testosterone therapy and after dose increases.

5.14 Hypercalcemia

Androgens, including TESTIM, should be used with caution in cancer patients at risk of hypercalcemia (and associated hypercalciuria). Regular monitoring of serum calcium concentrations is recommended in these patients.

5.15 Decreased Thyroxine-binding Globulin

Androgens, including TESTIM, may decrease concentrations of thyroxine-binding globulins, resulting in decreased total T4 serum concentrations and increased resin uptake of T3 and T4. Free thyroid hormone concentrations remain unchanged, however, and there is no clinical evidence of thyroid dysfunction.

5.16 Flammability

Alcohol-based products, including TESTIM, are flammable; therefore, patients should be advised to avoid fire, flame or smoking until the TESTIM has dried.

6 ADVERSE REACTIONS

6.1 Clinical Studies Experience

Because clinical trials are conducted under widely varying conditions, adverse reaction rates observed in the clinical trials of a drug cannot be directly compared to rates in the clinical trials of another drug and may not reflect the rates observed in practice.

In a controlled clinical study, 304 patients were treated with TESTIM 50 mg or 100 mg or placebo gel for up to 90 days. Two hundred five (205) patients received TESTIM 50 mg or 100 mg daily and 99 patients received placebo. Subjects could be counted in both TESTIM treatment groups if they received both 50 mg and 100 mg at different points in the study and experienced an adverse reaction at both dose levels. Adverse reactions reported by ≥ 1% of the TESTIM patients and greater than placebo are listed in Table 1.

Table 1: Incidence of Adverse Reactions (Reported by ≥ 1% of the TESTIM Patients and Greater than Placebo) in the Controlled Clinical Trial Through 90 Days
Event | TESTIM 50 mg (n=103) | TESTIM 100 mg (n=149) | Placebo (n=99)
Application Site Reactions | 2% | 4% | 3%
Blood Pressure Increased | 1% | 1% | 0%
Gynecomastia | 1% | 0% | 0%
Headache | 1% | 1% | 0%
Hematocrit / hemoglobin Increased | 1% | 2% | 0%
Hot Flushes | 1% | 0% | 0%
Insomnia | 1% | 0% | 0%
Mood Swings | 1% | 0% | 0%
Smell Disorder | 1% | 0% | 0%
Spontaneous Penile Erection | 1% | 0% | 0%
Taste Disorder | 1% | 1% | 0%

The following adverse reactions occurred in fewer than 1% of patients but were greater in TESTIM groups compared to the placebo group: activated partial thromboplastin time prolonged, blood creatinine increased, prothrombin time prolonged, appetite increased, sensitive nipples, and acne.

In this clinical trial of TESTIM, 6 patients had adverse reactions that led to their discontinuation. These events included: depression with suicidal ideation, urinary tract infection, mood swings and hypertension. No TESTIM patients discontinued due to skin reaction. In one foreign Phase 3 trial, one subject discontinued due to a skin-related adverse reaction.

In the pivotal US and European Phase 3 trials combined, at the 50-mg dosage strength, the percentage of subjects reporting clinically notable increases in hematocrit or hemoglobin were similar to placebo. However, in the 100-mg dose group, 2.3% and 2.8% of patients had a clinically notable increase in hemoglobin (≥ 19 g/dL) or hematocrit (≥ 58%), respectively, compared to 1.0% and 1.5% of patients in the placebo group, respectively.

In the combined US and European open-label extension studies, approximately 140 patients received TESTIM for at least 6 months. The results from these studies are consistent with those reported for the US controlled clinical trial.

Blood Pressure Increases

In a 4-month clinical study, 24-hour ambulatory blood pressure monitoring (ABPM) was conducted on 225 patients. ABPM was conducted at baseline and at Week 16 of TESTIM therapy. A total of 113 patients had acceptable ABPM recordings at both baseline and Week 16 and were at least 85% compliant with study drug. In that group, the mean change in 24-hour systolic blood pressure (BP) and diastolic BP from baseline to end-of-treatment at Week 16 (n=113) was 2.7 mm Hg (95% CI 0.7, 4.8) and 1.1 mm Hg (95% CI -0.1, 2.3), respectively. In patients with a history of hypertension who were receiving antihypertensive therapy, the mean ABPM systolic and diastolic BP increased by 1.9 mm Hg [95% CI -1.4, 5.2] and 0.3 mm Hg [95% CI -1.6, 2.2], respectively [n=55]). In patients with no history of hypertension, the mean systolic and diastolic blood pressure increased by 2.2 mm Hg [95% CI -0.4, 4.9] and 1.1 mm Hg [95% CI -0.4, 2.7], respectively [n=56].

3 patients (2.7%) on TESTIM, all of whom were receiving antihypertensive medications at baseline, either started new antihypertensive medications (n=3) or had their antihypertensive medication regimen adjusted (n=0) during the ABPM study.

Of the 225 patients in the ABPM study who used TESTIM, 6 patients (2.7%) were reported to have either an adverse reaction of hypertension (6 patients, 2.7%) or increased blood pressure (0 patients, 0.0%).

Cardiovascular Outcomes

TRAVERSE was a randomized, double-blind, cardiovascular outcomes study to assess the cardiovascular (CV) safety of topical testosterone gel compared to placebo in 5198 hypogonadal men aged 45 to 80 years with a history of CV disease or with multiple CV risk factors. The primary outcome was the incidence of the composite endpoint of major adverse cardiovascular events (MACE), consisting of CV death, non-fatal myocardial infarction (MI), and non-fatal stroke.

The mean duration of therapy was approximately 22 months. The mean duration of follow-up was 33 months. Approximately 61% of all patients discontinued topical testosterone gel or placebo therapy.

The mean patient age (±SD) was 63.3 (7.9) years, with 2452 patients aged 65 years or more (47%); 2847 (about 55%) patients had pre-existing cardiovascular disease, whereas 2357 patients (about 45%) had an elevated cardiovascular risk at baseline, and mean BMI was 35kg/m^2. Approximately 80% of patients were White, 17% were Black, and 3% were of other races or ethnic groups. Approximately 69%, 84%, and 93% had diabetes mellitus, hyperlipidemia, and hypertension, respectively.

The mean serum testosterone concentration at baseline in patients receiving topical testosterone gel was 220.4 ng/dL (n=2596). The mean serum testosterone concentrations at 12 months, 24 months, 36 months, and 48 months in patients receiving topical testosterone gel were 440.5 ng/dL (n=1683), 420.9 ng/dl (n=1125), 428.7 ng/dL (n=731), and 365.2 ng/dL (n=220), respectively.

For patients treated with topical testosterone gel, the incidence of MACE was 7.0% (n=182 events) and for those receiving placebo, the incidence of MACE was 7.3% (n=190 events). The study demonstrated non-inferiority of topical testosterone gel versus placebo because the upper bound of 95% CI was less than the pre-specified risk margin, of 1.5 for MACE (Hazard Ratio 0.96 [95% CI: 0.78, 1.17]).

Additional Adverse Reactions Reported in TRAVERSE

Additional adverse reactions reported in TRAVERSE at an incidence rate >2% in either treatment group and greater in topical testosterone gel versus placebo included: nonfatal arrythmias warranting intervention (5.2% vs 3.3%), atrial fibrillation (3.5% vs 2.4%), acute kidney injury (2.3% vs 1.5%) and bone fracture (3.5% vs 2.5%). For the adverse reaction of bone fracture, each event was adjudicated by clinical review.

6.2 Postmarketing Experience

The following adverse reactions have been identified during post-approval use of testosterone gel products. Because the reactions are reported voluntarily from a population of uncertain size, it is not always possible to reliably estimate their frequency or establish a causal relationship to drug exposure.

Secondary Exposure to Testosterone in Children

Cases of secondary exposure to testosterone resulting in virilization of children have been reported in postmarketing surveillance of testosterone gel products. Signs and symptoms of these reported cases have included enlargement of the clitoris (with surgical intervention) or of the penis, development of pubic hair, increased erections and libido, aggressive behavior, and advanced bone age. In most cases with a reported outcome, these signs and symptoms were reported to have regressed with removal of the testosterone gel exposure. In a few cases, however, enlarged genitalia did not fully return to age-appropriate normal size, and bone age remained modestly greater than chronological age. In some of the cases, direct contact with the sites of application on the skin of men using testosterone gel was reported. In at least one reported case, the reporter considered the possibility of secondary exposure from items such as the testosterone gel user’s shirts and/or other fabric, such as towels and sheets [see Warnings and Precautions (5.1)].

Vascular Disorders

Venous thromboembolism [see Warnings and Precautions (5.3)]

Cardiovascular Disorders

Myocardial infarction, stroke [see Warnings and Precautions (5.5)]

Blood and Lymphatic Disorders

Polycythemia [see Warnings and Precautions (5.2)]

7 DRUG INTERACTIONS

7.1 Insulin

Changes in insulin sensitivity or glycemic control may occur in patients treated with androgens. In diabetic patients, the metabolic effects of androgens may decrease blood glucose and, therefore, may necessitate a decrease in the dose of anti-diabetic medication.

7.2 Oral Anticoagulants

Changes in anticoagulant activity may be seen with androgens, therefore more frequent monitoring of international normalized ratio (INR) and prothrombin time are recommended in patients taking warfarin, especially at the initiation and termination of androgen therapy.

7.3 Corticosteroids

The concurrent use of testosterone with corticosteroids may result in increased fluid retention and requires careful monitoring particularly in patients with cardiac, renal or hepatic disease.

8 USE IN SPECIFIC POPULATIONS

8.1 Pregnancy

Risk Summary

TESTIM is contraindicated in pregnant women. Testosterone is teratogenic and may cause fetal harm based on data from animal studies and its mechanism of action [see Contraindications (4) and Clinical Pharmacology (12.1)]. Exposure of a female fetus to androgens may result in varying degrees of virilization. In animal development studies, exposure to testosterone in utero resulted in hormonal and behavioral changes in offspring and structural impairments of reproductive tissues in female and male offspring. These studies did not meet current standards for nonclinical development toxicity studies.

Data

Animal Data

In developmental studies conducted in rats, rabbits, pigs, sheep, and rhesus monkeys, pregnant animals received intramuscular injection of testosterone during the period of organogenesis. Testosterone treatment at doses that were comparable to those used for testosterone replacement therapy resulted in structural impairments in both female and male offspring. Structural impairments observed in females included increased anogenital distance, phallus development, empty scrotum, no external vagina, intrauterine growth retardation, reduced ovarian reserve, and increased ovarian follicular recruitment. Structural impairments seen in male offspring included increased testicular weight, larger seminal tubular lumen diameter, and higher frequency of occluded tubule lumen. Increased pituitary weight was seen in both sexes.

Testosterone exposure in utero also resulted in hormonal and behavioral changes in offspring. Hypertension was observed in pregnant female rats and their offspring exposed to doses approximately twice those used for testosterone replacement therapy.

8.2 Lactation

Risk Summary

TESTIM is not indicated for use in females.

8.3 Females and Males of Reproductive Potential

Infertility

During treatment with large doses of exogenous androgens, including TESTIM, spermatogenesis may be suppressed through feedback inhibition of the hypothalamic-pituitary-testicular axis [see Warnings and Precautions (5.8)], possible leading to adverse effects on semen parameters including sperm count. Reduced fertility is observed in some men taking testosterone replacement therapy. Testicular atrophy, subfertility, and infertility have also been reported in men who abuse anabolic androgenic steroids [see Drug Abuse and Dependence (9.2)]. With either type of use, the impact on fertility may be irreversible.

8.4 Pediatric Use

The safety and effectiveness of TESTIM in pediatric patients less than 18 years old have not been established. Improper use may result in acceleration of bone age and premature closure of epiphyses.

8.5 Geriatric Use

There is insufficient long-term safety data in geriatric patients to assess the potentially increased risks of cardiovascular disease and prostate cancer [see Warnings and Precautions (5.4)].

8.6 Renal Impairment

No studies were conducted in patients with renal impairment.

8.7 Hepatic Impairment

No studies were conducted in patients with hepatic impairment.

9 DRUG ABUSE AND DEPENDENCE

9.1 Controlled Substance

TESTIM contains testosterone, a Schedule III controlled substance in the Controlled Substances Act.

9.2 Abuse

Drug abuse is intentional non-therapeutic use of a drug, even once, for its rewarding psychological and physiological effects. Abuse and misuse of testosterone are seen in male and female adults and adolescents. Testosterone, often in combination with other anabolic androgenic steroids (AAS), and not obtained by prescription through a pharmacy, may be abused by athletes and bodybuilders. There have been reports of misuse of men taking higher doses of legally obtained testosterone than prescribed and continuing testosterone despite adverse events or against medical advice.

Abuse-Related Adverse Reactions

Serious adverse reactions have been reported in individuals who abuse anabolic androgenic steroids, and include cardiac arrest, myocardial infarction, hypertrophic cardiomyopathy, congestive heart failure, cerebrovascular accident, hepatotoxicity, and serious psychiatric manifestations, including major depression, mania, paranoia, psychosis, delusions, hallucinations, hostility, and aggression.

The following adverse reactions have also been reported in men: transient ischemic attacks, convulsions, hypomania, irritability, dyslipidemias, testicular atrophy, subfertility, and infertility.

The following additional adverse reactions have been reported in women: hirsutism, virilization, deepening of voice, clitoral enlargement, breast atrophy, male-pattern baldness, and menstrual irregularities.

The following adverse reactions have been reported in male and female adolescents: premature closure of bony epiphyses with termination of growth, and precocious puberty.

Because these reactions are reported voluntarily from a population of uncertain size and may include abuse of other agents, it is not always possible to reliably estimate their frequency or establish a causal relationship to drug exposure.

9.3 Dependence

Behaviors Associated with Addiction

Continued abuse of testosterone and other anabolic steroids, leading to addiction is characterized by the following behaviors:

- Taking greater dosages than prescribed
- Continued drug use despite medical and social problems due to drug use
- Spending significant time to obtain the drug when supplies of the drug are interrupted
- Giving a higher priority to drug use than other obligations
- Having difficulty in discontinuing the drug despite desires and attempts to do so
- Experiencing withdrawal symptoms upon abrupt discontinuation of use

Physical dependence is characterized by withdrawal symptoms after abrupt drug discontinuation or a significant dose reduction of a drug. Individuals taking supratherapeutic doses of testosterone may experience withdrawal symptoms lasting for weeks or months which include depressed mood, major depression, fatigue, craving, restlessness, irritability, anorexia, insomnia, decreased libido and hypogonadotropic hypogonadism.

Drug dependence in individuals using approved doses of testosterone for approved indications has not been documented.

10 OVERDOSAGE

There were no reports of overdose in the TESTIM clinical trials. There is a single report in the literature of acute overdosage after injection of testosterone enanthate. This subject had serum testosterone concentrations of up to 11,400 ng/dL, which were implicated in a cerebrovascular accident.

Treatment of overdosage would consist of discontinuation of TESTIM, washing the application site with soap and water, and appropriate symptomatic and supportive care.

11 DESCRIPTION

TESTIM (testosterone gel) is a clear to translucent hydroalcoholic topical gel containing testosterone, an androgen. TESTIM provides continuous transdermal delivery of testosterone for 24 hours, following a single application to intact, clean, dry skin of the shoulders and/or upper arms.

One 5-g or two 5-g tubes of TESTIM contains 50 mg or 100 mg of testosterone, respectively, to be applied daily to the skin’s surface. Approximately 10% of the applied testosterone dose is absorbed across skin of average permeability during a 24-hour period.

The active pharmacological ingredient in TESTIM is testosterone. Testosterone USP is a white to practically white crystalline powder chemically described as 17-β hydroxyandrost-4-en-3-one. The structural formula is shown in the following figure:

Testim may have an alcoholic/musk odor. Inactive ingredients in TESTIM are purified water, pentadecalactone, carbopol, acrylates, propylene glycol, glycerin, polyethylene glycol, ethanol (74%), and tromethamine.

12 CLINICAL PHARMACOLOGY

12.1 Mechanism of Action

Endogenous androgens, including testosterone and dihydrotestosterone (DHT), are responsible for the normal growth and development of the male sex organs and for maintenance of secondary sex characteristics. These effects include the growth and maturation of prostate, seminal vesicles, penis and scrotum; the development of male hair distribution, such as facial, pubic, chest and axillary hair; laryngeal enlargement; vocal cord thickening; and alterations in body musculature and fat distribution. Testosterone and DHT are necessary for the normal development of secondary sex characteristics.

Male hypogonadism, a clinical syndrome resulting from insufficient secretion of testosterone, has 2 main etiologies. Primary hypogonadism is caused by defects of the gonads, such as Klinefelter's syndrome or Leydig cell aplasia, while secondary hypogonadism (hypogonadotropic hypogonadism) is the failure of the hypothalamus (or pituitary) to produce sufficient gonadotropins (FSH, LH).

12.2 Pharmacodynamics

No specific pharmacodynamic studies were conducted using TESTIM.

12.3 Pharmacokinetics

Absorption

TESTIM (testosterone gel) delivers physiologic amounts of testosterone, producing circulating testosterone concentrations that approximate normal concentrations (e.g., 300 – 1000 ng/dL) seen in healthy men.

The skin serves as a reservoir for the sustained release of testosterone into the systemic circulation. Approximately 10% of the testosterone applied on the skin surface is absorbed into the systemic circulation during a 24-hour period.

Single Dose

In single-dose studies, when either TESTIM 50 mg or 100 mg was administered, absorption of testosterone into the blood continued for the entire 24-hour dosing period. Also, mean peak and average serum concentrations within the normal range were achieved within 24 hours.

Multiple Dose

With single daily applications of TESTIM 50 mg and 100 mg, follow-up measurements at 30 and 90 days after starting treatment have confirmed that serum testosterone and DHT concentrations are generally maintained within the normal range.

Figure 1 summarizes the 24-hour pharmacokinetic profile of testosterone for patients maintained on TESTIM 50 mg or TESTIM 100 mg for 30 days.

Figure 1:
Mean Steady-State Serum Testosterone (± SD) (ng/dL) Concentrations on Day 30 in Patients Applying TESTIM Once Daily

The average daily testosterone concentration produced by TESTIM 100 mg at Day 30 was 612 (± 286) ng/dL and by TESTIM 50 mg at Day 30 was 365 (± 187) ng/dL.

Distribution

Circulating testosterone is primarily bound in the serum to sex hormone-binding globulin (SHBG) and albumin. Approximately 40% of testosterone in plasma is bound to SHBG, 2% remains unbound (free) and the rest is loosely bound to albumin and other proteins.

Metabolism

Testosterone is metabolized to various 17-keto steroids through 2 different pathways. The major active metabolites of testosterone are estradiol and DHT. The average daily DHT concentration produced by TESTIM 100 mg at Day 30 was 555 (± 293) pg/mL and by TESTIM 50 mg at Day 30 was 346 (± 212) pg/mL.

Figure 2 summarizes the 24-hour pharmacokinetic profile of DHT for patients maintained on TESTIM 50 mg or TESTIM 100 mg for 30 days.

Figure 2:
Mean Steady-State Serum Dihydrotestosterone (± SD) (pg/mL) Concentrations on Day 30 in Patients Applying TESTIM Once Daily

Excretion

There is considerable variation in the half-life of testosterone concentration as reported in the literature, ranging from 10 to 100 minutes. About 90% of a dose of testosterone given intramuscularly is excreted in the urine as glucuronic acid and sulfuric acid conjugates of testosterone and its metabolites. About 6% of a dose is excreted in the feces, mostly in the unconjugated form. Inactivation of testosterone occurs primarily in the liver.

Potential for Testosterone Transfer from Male Patients to Female Partners

The potential for dermal testosterone transfer following TESTIM use was evaluated in two clinical trials with males dosed with TESTIM and their untreated female partners.

In the first trial, 30 couples were evenly randomized to 5 groups. In the first 4 groups, 100 mg of TESTIM was applied to the male abdomen and the couples were then asked to rub abdomen-to-abdomen for 15 minutes at 1 hour, 4 hours, 8 hours, or 12 hours after dose application, respectively. In these couples, serum testosterone concentrations in female partners increased from baseline by at least 6 times and potential for transfer was seen at all time points.

When 6 males used a shirt to cover the abdomen at 15 minutes post-application and partners again rubbed abdomens for 15 minutes at the 1-hour time point, serum testosterone concentrations in female partners increased from baseline by approximately 3 times.

In the second trial, 24 couples were evenly randomized to 4 groups. TESTIM 100 mg was applied to the male upper arms and shoulders. In one group, 15 minutes of direct skin-to-skin rubbing began at 4 hours after application. In these 6 women, all of whom showered immediately after the rubbing activity, mean maximum serum testosterone concentrations increased from baseline by approximately 4 times. When males wore a long-sleeved T-shirt and rubbing was started at 1 and at 4 hours after application, the transfer of testosterone from male to female partners was prevented.

Effect of Showering

The effect of showering (with mild soap) at 1, 2, and 6 hours post application of TESTIM 100 mg was evaluated in a clinical trial in 12 men. The study demonstrated that the overall effect of washing was to decrease testosterone concentrations; however, when washing occurred 2 or more hours post drug application, serum testosterone concentrations remained within the normal range.

13 NONCLINICAL TOXICOLOGY

13.1 Carcinogenesis, Mutagenesis, Impairment of Fertility

Carcinogenesis

Testosterone has been tested by subcutaneous injection and implantation in mice and rats. In mice, the implant induced cervical-uterine tumors, which metastasized in some cases. There is suggestive evidence that injection of testosterone into some strains of female mice increases their susceptibility to hepatoma. Testosterone is also known to increase the number of tumors and decrease the degree of differentiation of chemically induced carcinomas of the liver in rats.

Mutagenesis

Testosterone was negative in the in vitro Ames and in the in vivo mouse micronucleus assays.

Impairment of Fertility

The administration of exogenous testosterone has been reported to suppress spermatogenesis in the rat, dog, and non-human primates, which was reversible on cessation of the treatment.

14 CLINICAL STUDIES

14.1 Clinical Trials in Adult Hypogonadal Males

TESTIM was evaluated in a randomized multicenter, multi-dose, active and placebo controlled 90-day study in 406 adult males with morning testosterone concentrations ≤ 300 ng/dL. The study was double-blind for the doses of TESTIM and placebo, but open-label for the non-scrotal testosterone transdermal system. During the first 60 days, patients were evenly randomized to TESTIM 50 mg, TESTIM 100 mg, placebo gel, or testosterone transdermal system. At Day 60, patients receiving TESTIM were maintained at the same dose, or were titrated up or down within their treatment group, based on 24-hour averaged serum testosterone concentration obtained on Day 30.

Of 192 hypogonadal men who were appropriately titrated with TESTIM and who had sufficient data for analysis, 74% achieved an average serum testosterone concentration within the normal range (300 to 1,000 ng/dL) on treatment Day 90.

Table 2 summarizes the mean testosterone concentrations on Day 30 for patients receiving TESTIM 50 mg or 100 mg.

Table 2: Mean (± SD) Steady-State Serum Testosterone Concentrations on Day 30
 | TESTIM 50 mg (n=94) | TESTIM 100 mg (n=95) | Placebo (n=93)
Cavg (ng/dL) | 365 ± 187 | 612 ± 286 | 216 ± 79
Cmax (ng/dL) | 538 ± 371 | 897 ± 565 | 271 ± 110
Cmin (ng/dL) | 223 ± 126 | 394 ±189 | 164 ± 64

16 HOW SUPPLIED/STORAGE AND HANDLING

TESTIM is supplied in unit-dose tubes in cartons of 30. Each tube contains 50 mg testosterone in 5 g of gel, and is supplied as follows:

NDC Number | Package Size
66887-001-05 | 30 tubes: 50 mg testosterone in 5 g of gel per tube

STORAGE AND HANDLING

Store at 20°C to 25°C (68°F to 77°F). Excursions permitted to 15°C to 30°C (59°F to 86°F) [See USP Controlled Room Temperature].

Discard used TESTIM tubes in household trash in a manner that prevents accidental exposure of women, children, or pets [see Boxed Warning and Warnings and Precautions (5.1)]. Contents are flammable [see Warnings and Precautions (5.16)].

17 PATIENT COUNSELING INFORMATION

Advise the patient to read the FDA-approved patient labeling (Medication Guide).

Advise patients of the following:

17.1 Men with Known or Suspected Carcinoma of the Breast or Prostate

Men with known or suspected prostate or breast cancer should not use TESTIM [see Contraindications (4) and Warnings and Precautions (5.4)].

17.2 Potential for Secondary Exposure to Testosterone and Steps to Prevent Secondary Exposure

Secondary exposure to testosterone in children and women can occur with the use of testosterone gel in men. Cases of secondary exposure to testosterone have been reported in children.

Physicians should advise patients of the reported signs and symptoms of secondary exposure which may include the following:

- In children; unexpected sexual development including inappropriate enlargement of the penis or clitoris, premature development of pubic hair, increased erections, and aggressive behavior
- In women; changes in hair distribution, increase in acne, or other signs of testosterone effects
- The possibility of secondary exposure to TESTIM should be brought to the attention of a healthcare provider
- TESTIM should be promptly discontinued until the cause of virilization is identified

Strict adherence to the following precautions is advised to minimize the potential for secondary exposure to testosterone from TESTIM in men [see Medication Guide]:

- Children and women should avoid contact with unwashed or unclothed application site(s) of men using TESTIM.
- Patients using TESTIM should apply the product as directed and strictly adhere to the following:

- Wash hands with soap and water immediately after application.

- Cover the application site(s) with clothing after the gel has dried.

- Wash the application site(s) thoroughly with soap and water prior to any situation where skin-to-skin contact of the application site with another person is anticipated.

- In the event that unwashed or unclothed skin to which TESTIM has been applied comes in contact with the skin of another person, the general area of contact on the other person should be washed with soap and water as soon as possible [see Dosage and Administration (2.2), Warnings and Precautions (5.1), and Clinical Pharmacology (12.3)].

17.3 Potential Adverse Reactions with Androgens

Patients should be informed that treatment with androgens may lead to adverse reactions which include:

- Changes in urinary habits, such as increased urination at night, trouble starting the urine stream, passing urine many times during the day, having an urge to go the bathroom right away, having a urine accident, or being unable to pass urine or weak urine flow
- Breathing disturbances, including those associated with sleep or excessive daytime sleepiness
- Too frequent or persistent erections of the penis
- Nausea, vomiting, changes in skin color, or ankle swelling
- Venous thromboembolism, the signs and symptoms of which may include lower limb pain, edema, or erythema; dyspnea; or chest pain.
- Increased blood pressure that can increase cardiovascular risk over time.

17.4 Patients Should Be Advised of the Following Instructions for Use

- Read the Medication Guide before starting TESTIM therapy and reread it each time the prescription is renewed.
- TESTIM should be applied and used appropriately to maximize the benefits and to minimize the risk of secondary exposure in children and women.
- Keep TESTIM out of the reach of children. The package is not child resistant.
- TESTIM is an alcohol-based product and is flammable; therefore avoid fire, flame or smoking until the gel has dried.
- It is important to adhere to all recommended monitoring.
- Report any changes in their state of health, such as changes in urinary habits, breathing, sleep, and mood.
- TESTIM is prescribed to meet the patient’s specific needs; therefore, the patient should never share TESTIM with anyone.
- TESTIM should be applied once daily at approximately the same time each day to clean dry skin of the shoulders and/or upper arms.
- TESTIM should not be applied to the scrotum, penis, or abdomen.
- Wait 2 hours before swimming or washing following application of TESTIM. This will ensure that the greatest amount of TESTIM is absorbed into their system.

Manufactured for:
Endo USA
Malvern, PA 19355

Manufactured by:
DPT Laboratories, Ltd.
San Antonio, TX 78215

or

Contract Pharmaceuticals Limited
Mississauga, ON, Canada L5N 6R8

US Patent Nos. 7,320,968; 7,608,605; 7,608,606; 7,608,607; 7,608,608; 7,608,609; 7,608,610; 7,935,690; 8,063,029; 8,178,518

© 2025 Endo, Inc. or one of its affiliates.

Revised: 07/2025

MEDICATION GUIDE

Testim® (TĔS tim)

(testosterone gel) for topical use, CIII

What is the most important information I should know about Testim?

1. Testim can transfer from your body to others including, children and women. Children and women should avoid contact with the unwashed or not covered (unclothed) areas where Testim has been applied to your skin. Early signs and symptoms of puberty have occurred in young children who have come in direct contact with testosterone by touching areas where men have used Testim.

Children

Signs and symptoms of early puberty in a child when they come in direct contact with Testim may include:

Abnormal sexual changes:

- enlarged penis or clitoris.
- early growth of hair near the vagina or around the penis (pubic hair).
- erections or acting out sexual urges (sex drive).

Behavior problems:

- acting aggressively, behaving in an angry or violent way.

Women

Signs and symptoms in women when they come in direct contact with Testim may include:

- changes in body hair.
- an abnormal increase in pimples (acne).

Stop using Testim and call your healthcare provider right away if you see any signs and symptoms in a child or a woman that may have happened through accidental touching of the area where you have placed Testim.

2. To lower the risk of transfer of Testim from your body to others, follow these important instructions:

- Apply Testim only to the areas of your shoulders and upper arms that will be covered by a short sleeve t-shirt.
- Wash your hands right away with soap and water after applying Testim.
- After the gel has dried, cover the application area with clothing. Keep the area covered until you have washed the application area well or have showered.
- If you expect to have skin-to-skin contact with another person, first wash the application area well with soap and water.
- If a child or woman touches the area where you have applied Testim, that area on the child or woman should be washed well with soap and water right away.

What is Testim?

Testim is a prescription medicine that contains testosterone. Testim is used to treat adult males who have low or no testosterone due to certain medical conditions.

- Your healthcare provider will test your blood before you start and while you are using Testim.
- It is not known if Testim is safe or effective to treat men who have low testosterone due to aging.
- It is not known if Testim is safe or effective in children younger than 18 years old. Improper use of testosterone in children may affect bone growth.

Testim is a controlled substance (CIII) because it contains testosterone that can be a target for people who abuse prescription medicines. Keep your Testim in a safe place to protect it. Never give your Testim to anyone else, even if they have the same symptoms you have. Selling or giving away this medicine may harm others and it is against the law.

Testim is not meant for use in women.

Do not use Testim if you:

- have breast cancer.
- have or might have prostate cancer.
- are pregnant. Testim may harm your unborn baby.
- Women who are pregnant should avoid contact with the area of skin where Testim has been applied.

Before using Testim, tell your healthcare provider about all of your medical conditions including if you:

- have breast cancer.
- have or might have prostate cancer.
- have urinary problems due to an enlarged prostate.
- have high blood pressure or are being treated for high blood pressure
- have heart problems.
- have liver or kidney problems.
- have problems breathing while you sleep (sleep apnea).

Tell your healthcare provider about all the medicines you take, including prescription and over-the-counter medicines, vitamins, and herbal supplements. Using Testim with certain other medicines can affect each other. Especially, tell your healthcare provider if you take:

- insulin
- medicines that decrease blood clotting (blood thinners)
- corticosteroids

How should I use Testim?

- See the detailed Instructions for Use for information about how to use Testim at the end of this Medication Guide.
- It is important that you apply Testim exactly as your healthcare provider tells you to.
- Your healthcare provider may change your Testim dose. Do not change your Testim dose without talking to your healthcare provider.
- Apply Testim at the same time each morning. Testim should be applied after showering or bathing.

What are the possible side effects of Testim?

Testim can cause serious side effects including:

See “What is the most important information I should know about Testim?”

- If you already have enlargement of your prostate gland your signs and symptoms can get worse while using Testim. This can include:
  - increased urination at night.
  - trouble starting your urine stream.
  - having to pass urine many times during the day.
  - having an urge to go to the bathroom right away.
  - having a urine accident.

- being unable to pass urine or weak urine flow.

- Possible increased risk of prostate cancer. Your healthcare provider should check you for prostate cancer or any other prostate problems before you start and while you use Testim.
- Blood clots in the legs or lungs. Signs and symptoms of a blood clot in your leg can include leg pain, swelling or redness. Signs and symptoms of a blood clot in your lungs can include difficulty breathing or chest pain.
- Increased blood pressure. TESTIM can increase your blood pressure, which can increase your risk of having a heart attack or stroke over time. Your risk may be greater if you have already had a heart attack or stroke or if you have other risk factors for heart attack or stroke. You may need to start new medicines or have medicines changed for high blood pressure while on TESTIM. If your blood pressure cannot be controlled, TESTIM may need to be stopped. Your healthcare provider should check your blood pressure while you use TESTIM.
- In large doses Testim may lower your sperm count.
- Swelling of your ankles, feet, or body, with or without heart failure. This may cause serious problems for people who have heart, kidney or liver disease.
- Enlarged or painful breasts.
- Having problems breathing while you sleep (sleep apnea).

Call your healthcare provider right away if you have any of the serious side effects listed above.

The most common side effects of Testim include:

- skin irritation where Testim is applied
- increased red blood cell count
- headache
- increased blood pressure

Other side effects include more erections than are normal for you or erections that last a long time.

Tell your healthcare provider if you have any side effect that bothers you or that does not go away.
These are not all the possible side effects of Testim. For more information, ask your healthcare provider or pharmacist.

Call your doctor for medical advice about side effects. You may report side effects to FDA at 1-800-FDA-1088.

How should I store Testim?

- Store Testim at room temperature between 68ºF and 77ºF (20ºC to 25ºC).
- Safely throw away used Testim in household trash. Be careful to prevent accidental exposure of children or pets.
- Keep Testim away from fire.

Keep Testim and all medicines out of the reach of children.

General information about the safe and effective use of Testim.

Medicines are sometimes prescribed for purposes other than those listed in a Medication Guide. Do not use Testim for a condition for which it was not prescribed. Do not give Testim to other people, even if they have the same symptoms that you have. It may harm them.

You can ask your pharmacist or healthcare provider for information about Testim that is written for health professionals.

What are the ingredients in Testim?

Active ingredient: testosterone

Inactive ingredients: purified water, pentadecalactone, carbopol, acrylates, propylene glycol, glycerin, polyethylene glycol, ethanol (74%), and tromethamine.

Manufactured for:; Endo USA; Malvern, PA 19355 | Manufactured by:; DPT Laboratories, Ltd.; San Antonio, TX 78215
or
Contract Pharmaceuticals Limited
Mississauga, ON
Canada L5N 6R8

© 2025 Endo, Inc. or one of its affiliates.

For more information, go to www.TESTIM.com or call 1-800-462-3636.

This Medication Guide has been approved by the U.S. Food and Drug Administration.

Revised: 07/2025

INSTRUCTIONS FOR USE

Testim® (TĔS tim)

(testosterone gel)

for topical use, CIII

Read this Instructions for Use for Testim before you start using it and each time you get a refill. There may be new information. This leaflet does not take the place of talking to your healthcare provider about your medical condition or treatment.

Important Information about Testim:

- Children and women should avoid contact with the unwashed or not covered (unclothed) areas where Testim has been applied to your skin. If a child or woman touches the area where you have applied Testim, that area on the child or woman should be washed well with soap and water right away.
- If you expect to have skin-to-skin contact with another person, first wash the application area well with soap and water.
- Testim is flammable until dry. Let the Testim dry before smoking or going near an open flame.
- Before applying Testim, make sure that your shoulders and upper arms are clean, dry, and there is no broken skin.
- The application sites for Testim are the shoulders and upper arms that will be covered by a short sleeve t-shirt (see Figure A). Do not apply Testim to any other parts of your body such as your stomach area (abdomen), penis, or scrotum.

Applying Testim:

- Remove the cap from the tube and use the top of the cap to pierce the metal seal on the top of the tube by pushing or screwing the cap in.
- Testim may have an alcoholic or musk odor.
- Squeeze all of the Testim out of the tube by pushing or screwing the cap in.
- Apply all of the Testim to the application site. Rub the gel onto your skin for several seconds.
- Let the application site dry for a few minutes before putting on a t-shirt.
- Wash your hands with soap and water right away after applying Testim.
- Avoid showering, swimming, or bathing for at least 2 hours after you apply Testim.

How should I store Testim?

- Store Testim at room temperature between 68ºF to 77ºF (20ºC to 25ºC).
- Safely throw away used Testim in the household trash. Be careful to prevent accidental exposure of women, children or pets.
- Keep Testim away from fire.

Keep TESTIM and all medicines out of the reach of children.

This Instructions for Use has been approved by the U.S. Food and Drug Administration.

Revised: 08/2021